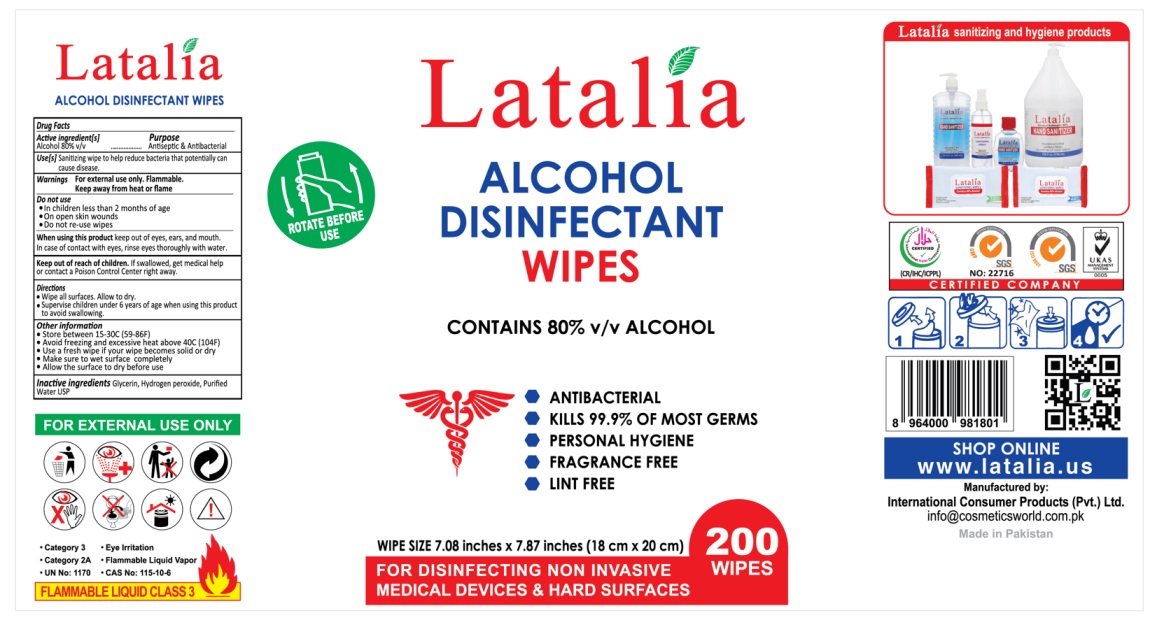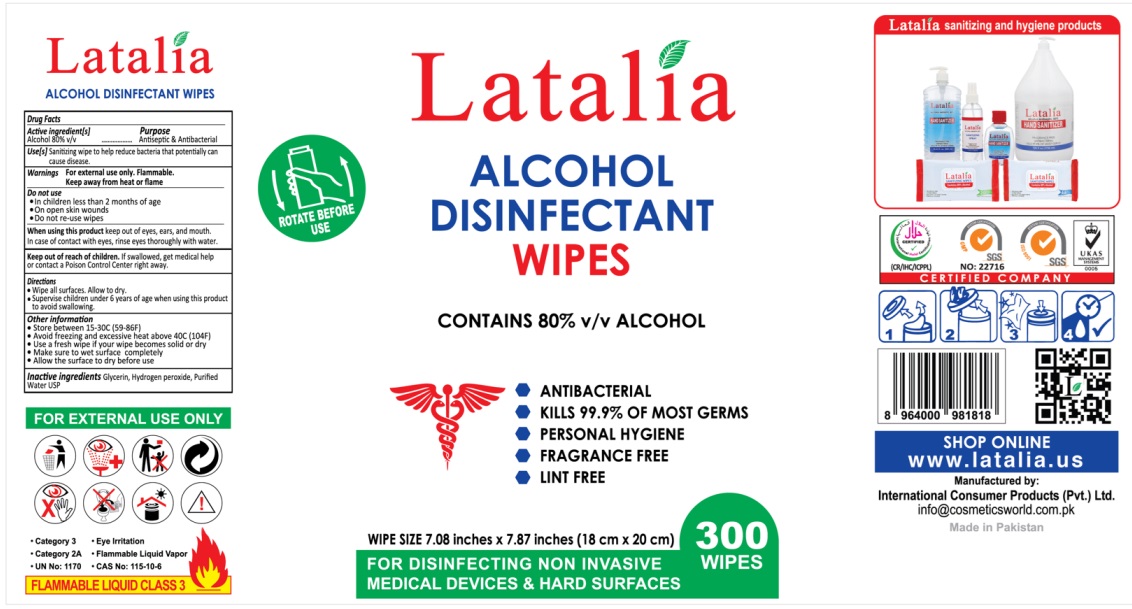 DRUG LABEL: Latalia alcohol disinfectant wipes
NDC: 80016-006 | Form: CLOTH
Manufacturer: INTERNATIONAL CONSUMER PRODUCTS (PVT.) LTD
Category: otc | Type: HUMAN OTC DRUG LABEL
Date: 20260203

ACTIVE INGREDIENTS: ALCOHOL 80 mL/100 mL
INACTIVE INGREDIENTS: GLYCERIN; HYDROGEN PEROXIDE; WATER

Active ingredient[s]

Alcohol 80% v/v

Purpose

Antiseptic & Antibacterial

Use[s]

Sanitizing wipe to help reduce bacteria that potentially can cause disease.

Warnings

For external use only. Flammable. Keep away from heat or flame

Do not use

- in children less than 2 months of age.
- on open skin wounds
- Do not re-use wipes

When using this product

keep out of eyes, ears, and mouth. In case of contact with eyes, rinse eyes thoroughly with water.

Keep out of reach of children.

If swallowed, get medical help or contact Poison Control Center right away.

Directions

- Wipe hands or all surfaces. Allow to dry.
- Supervise children under 6 years of age when using this product to avoid swallowing.

Other information

- Store between 15-30C (59-86F)
- Avoid freezing and excessive heat above 40C (104F)
- use fresh wipe if your wipe becomes solid or dry
- Make sure to wet surface completely
- Allow surface to dry before use

Inactive ingredients

Glycerin, Hydrogen peroxide, Purified Water USP.